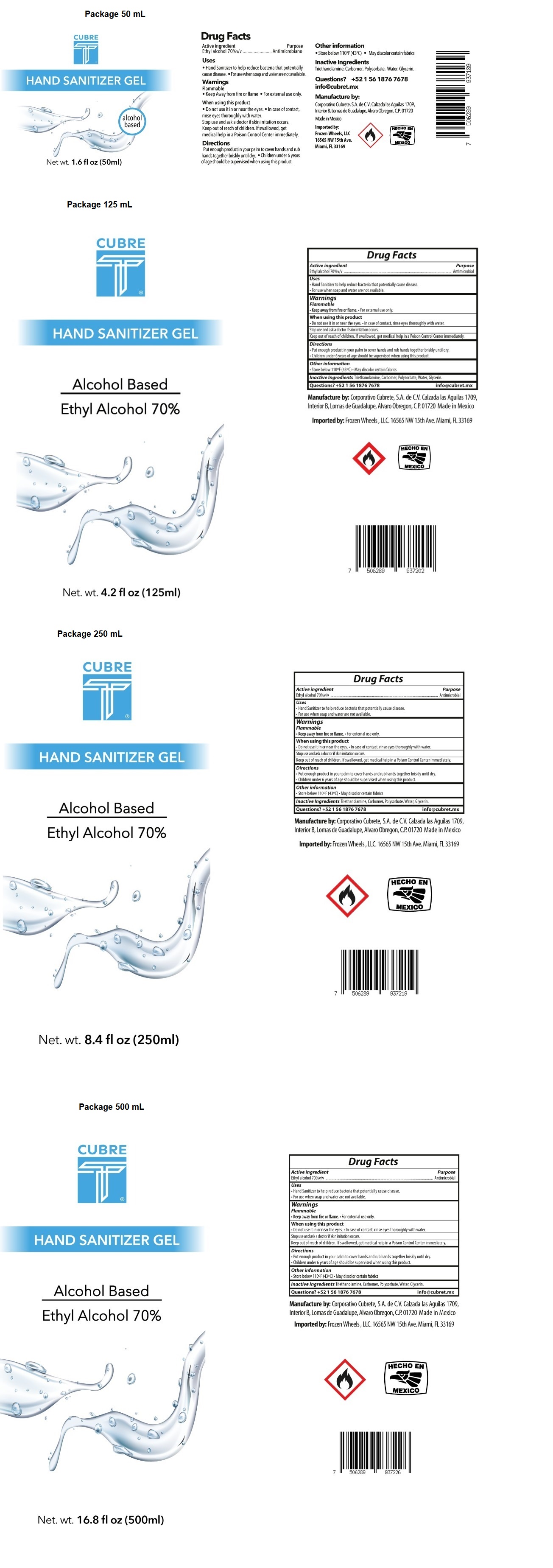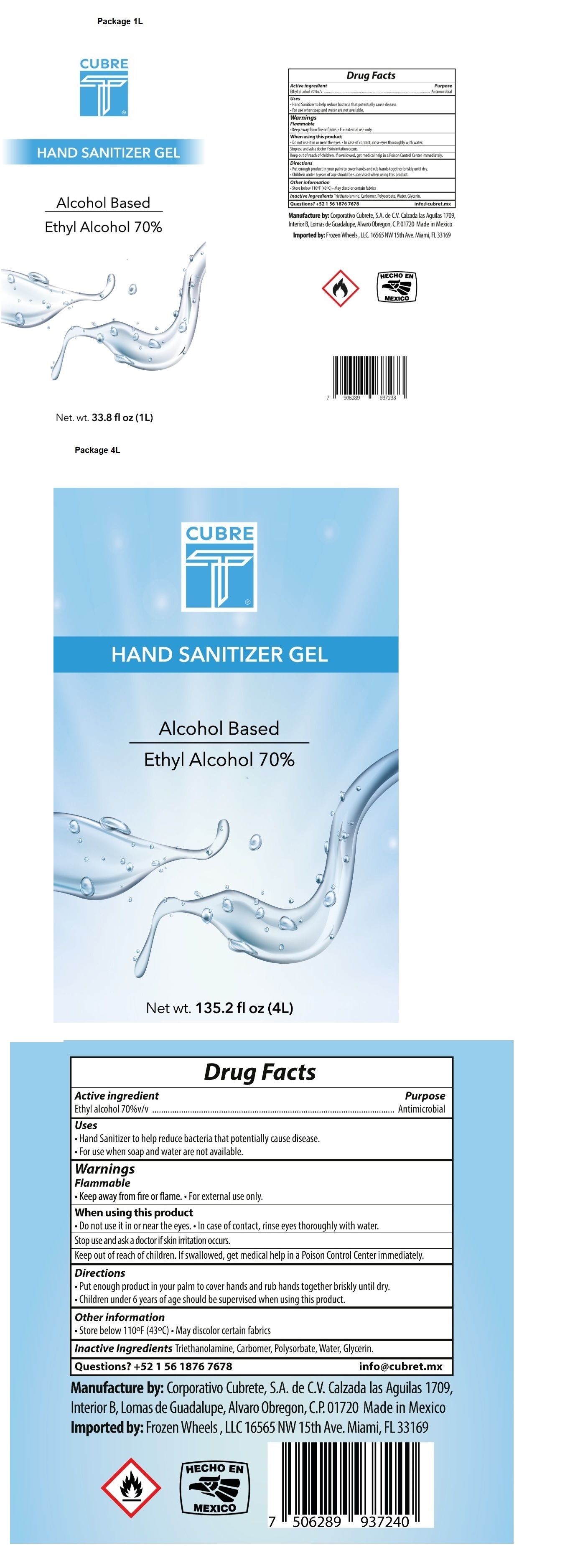 DRUG LABEL: CUBRETE ANTISEPTIC HAND SANITIZER
NDC: 77031-105 | Form: GEL
Manufacturer: Frozen Wheels, Llc
Category: otc | Type: HUMAN OTC DRUG LABEL
Date: 20200708

ACTIVE INGREDIENTS: ALCOHOL 70 mL/100 mL
INACTIVE INGREDIENTS: TROLAMINE; CARBOMER HOMOPOLYMER, UNSPECIFIED TYPE; POLYSORBATE 20; WATER; GLYCERIN

CUBRE T® HAND SANITIZER GEL

Active ingredient

Ethyl alcohol 70%v/v

Purpose

Antimicrobial

Uses

- Hand Sanitizer to help reduce bacteria that potentially cause disease.
- For use when soap and water are not available.

Warnings

Flammable

• Keep away from fire or flame. • For external use only.

When using this product

• Do not use it in or near the eyes. • In case of contact, rinse eyes thoroughly with water.

Stop use and ask a doctor if skin irritation occurs.

Keep out of reach of children. If swallowed, get medical help in a Poison Control Center immediately.

Directions

- Put enough product in your palm to cover hands and rub hands together briskly untill dry.
- Children under 6 years of age should be supervised when using this product.

Other information

• Store below 110°F (43°C) • May discolor certain fabrics

INACTIVE INGREDIENT

Inactive Ingredients Triethanolamine, Carbomer, Polysorbate, Water, Glycerin.

Questions?

+52 1 56 1876 7678 info@cubret.mx

Alcohol Based

Manufactured by: Corporativo Cubrete, S.A. de C.V. Calzada las Aguilas 1709, Interior B, Lomas de Guadalupe, Alvaro Obregon, C.P.01720 Made in Mexio

Imported by: Frozen Wheels, LLC 16565 NW 15th Ave. Miami, FL 33169

HECHO EN

MEXICO